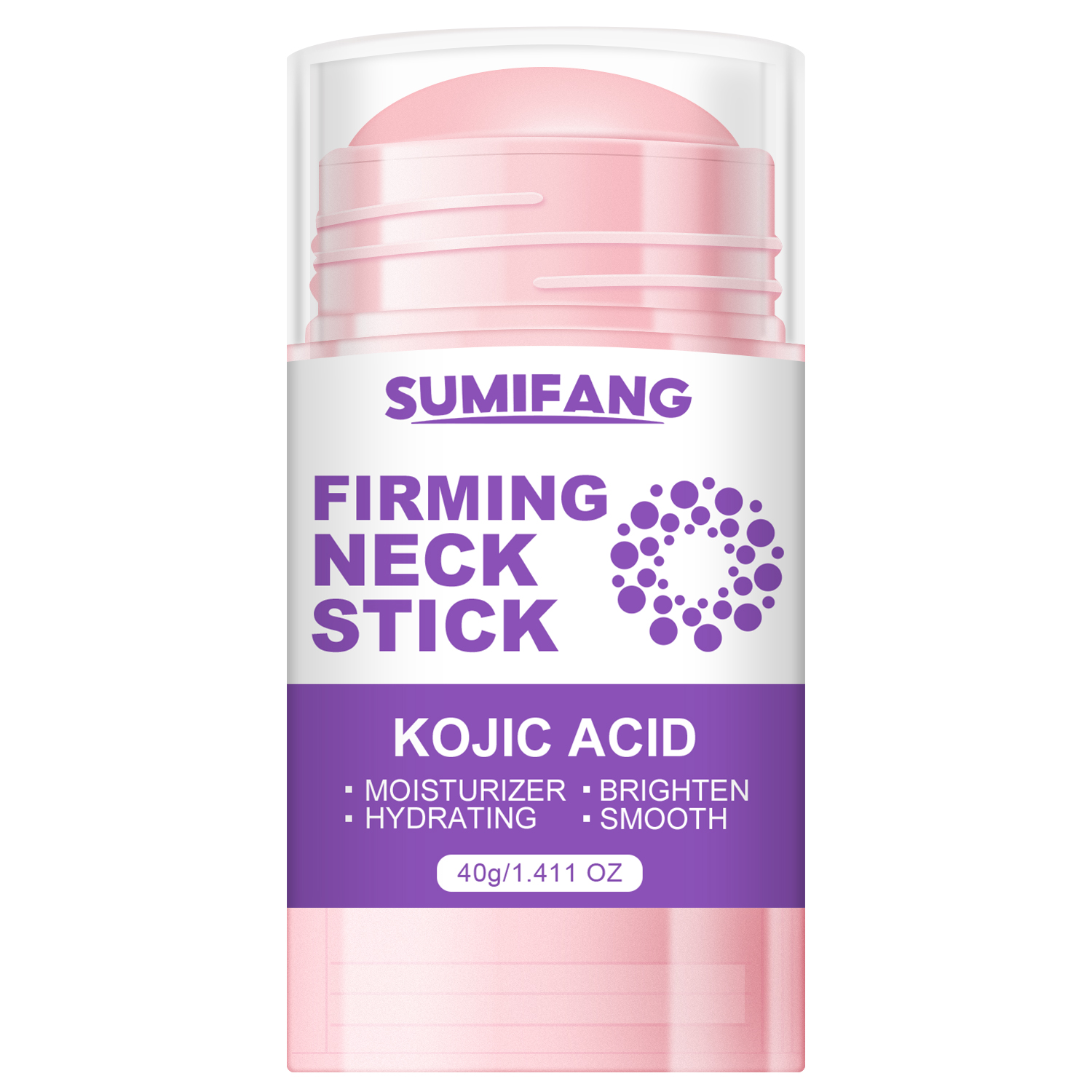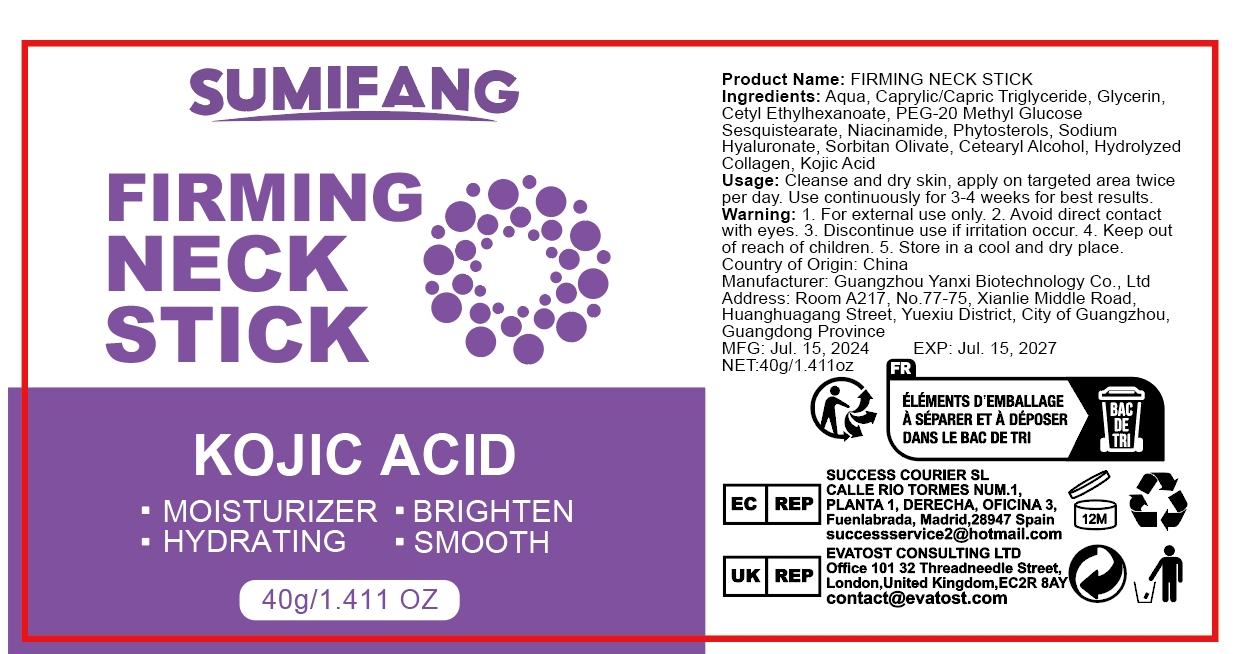 DRUG LABEL: Firming NeckStick
NDC: 84025-102 | Form: CREAM
Manufacturer: Guangzhou Yanxi Biotechnology Co.. Ltd
Category: otc | Type: HUMAN OTC DRUG LABEL
Date: 20240729

ACTIVE INGREDIENTS: MINERAL OIL 3 mg/40 g; KOJIC ACID 5 mg/40 g
INACTIVE INGREDIENTS: WATER

DOSAGE AND ADMINISTRATION

Stick for Neck Skin Care

WARNINGS

keep out of children

INACTIVE INGREDIENT

Aqua

INDICATIONS AND USAGE

For Neck Skin Treatment

keep out of children

PURPOSE

Nourishes and brightens the neck